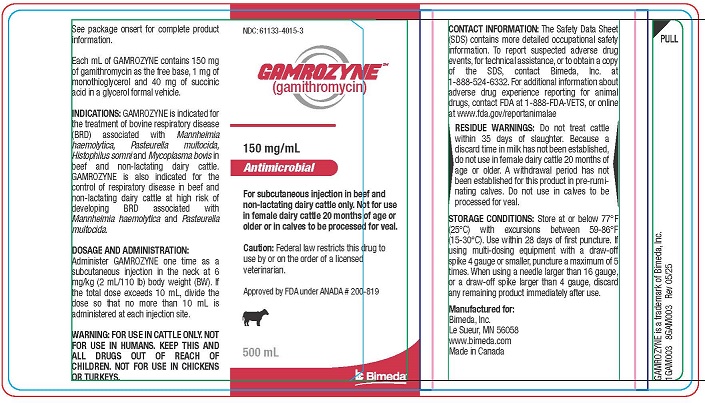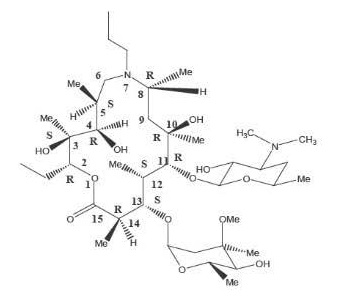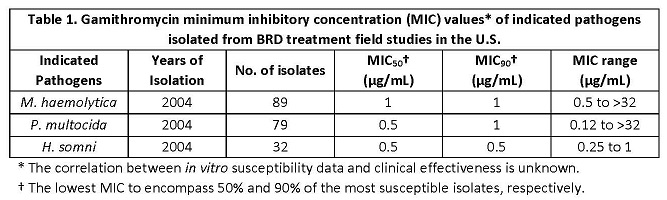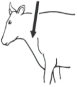 DRUG LABEL: GAMROZYNE
NDC: 61133-4015 | Form: INJECTION, SOLUTION
Manufacturer: Bimeda, Inc
Category: animal | Type: PRESCRIPTION ANIMAL DRUG LABEL
Date: 20250903

ACTIVE INGREDIENTS: GAMITHROMYCIN 150 mg/1 mL
INACTIVE INGREDIENTS: MONOTHIOGLYCEROL 1 mg/1 mL; SUCCINIC ACID 40 mg/1 mL; GLYCEROL FORMAL

GAMROZYNETM
(gamithromycin)

GAMROZYNETM
(gamithromycin)

150 mg/mL ANTIMICROBIAL
For subcutaneous injection in beef and non-lactating dairy cattle only. Not for use in female dairy cattle 20 months of age or older or in calves to be processed for veal.

Caution: Federal law restricts this drug to use by or on the order of a licensed veterinarian.

READ ENTIRE BROCHURE CAREFULLY BEFORE USING THIS PRODUCT

DESCRIPTION

GAMROZYNE Injection for Cattle is a ready to use sterile parenteral solution containing gamithromycin, a macrolide sub-class, 7a-azalide antimicrobial. Each mL of GAMROZYNE contains 150 mg of gamithromycin as the free base, 1 mg of monothioglycerol and 40 mg of succinic acid in a glycerol formal vehicle.
The chemical name of gamithromycin is 1-Oxa-7-azacyclopentadecan-15-one,13-[(2,6-dideoy-3-C-methyl-3-O-methyl-alpha-L-ribo-hexopyranosyl)oxy]-2-ethyl-3,4,10-trihydroxy 3,5,8,10,12,14-hexamethyl-7-propyl-11-{[3,4,6-trideoxy-3-(dimethylamino)-beta-D-xylo-hexopyranosyl]oxy}-, [(2R*,3S*,4R*,5S*,8R*,10R*, 11R*,12S*,13S*,14R*)]-and the structure is shown below.

INDICATIONS

GAMROZYNE is indicated for the treatment of bovine respiratory disease (BRD) associated with Mannheimia haemolytica, Pasteurella multocida, Histophilus somni and Mycoplasma bovis in beef and non-lactating dairy cattle. GAMROZYNE is also indicated for the control of respiratory disease in beef and non-lactating dairy cattle at high risk of developing BRD associated with Mannheimia haemolytica and Pasteurella multocida.

DOSAGE AND ADMINISTRATION

Administer GAMROZYNE one time as a subcutaneous injection in the neck at 6 mg/kg (2 mL/110 lb) body weight (BW). If the total dose exceeds 10 mL, divide the dose so that no more than 10 mL is administered at each injection site.

Body Weight (lb) | Dose Volume (mL)
110 | 2
220 | 4
330 | 6
440 | 8
550 | 10
660 | 12
770 | 14
880 | 16
990 | 18
1100 | 20

Animals should be appropriately restrained to achieve the proper route of administration. Use sterile equipment. Inject under the skin in front of the shoulder (see ILLUSTRATION).

CONTRAINDICATIONS

As with all drugs, the use of GAMROZYNE is contraindicated in animals previously found to be hypersensitive to this drug.

WARNING:

FOR USE IN CATTLE ONLY.
NOT FOR USE IN HUMANS.
KEEP THIS AND ALL DRUGS OUT OF REACH OF CHILDREN.
NOT FOR USE IN CHICKENS OR TURKEYS.

CONTACT INFORMATION

The Safety Data Sheet (SDS) contains more detailed occupational safety information. To report suspected adverse drug events, for technical assistance, or to obtain a copy of the SDS, contact Bimeda, Inc. at 1-888-524-6332. For additional information about adverse drug experience reporting for animal drugs, contact FDA at 1-888-FDA-VETS, or online at www.fda.gov/reportanimalae

RESIDUE WARNINGS

Do not treat cattle within 35 days of slaughter. Because a discard time in milk has not been established, do not use in female dairy cattle 20 months of age or older. A withdrawal period has not been established for this product in pre-ruminating calves. Do not use in calves to be processed for veal.

PRECAUTIONS

The effects of GAMROZYNE on bovine reproductive performance, pregnancy, and lactation have not been determined. Subcutaneous injection of GAMROZYNE may cause a transient local tissue reaction in some cattle that may result in trim loss of edible tissues at slaughter.

ADVERSE REACTIONS
Transient animal discomfort and mild to moderate injection site swelling may be seen in cattle treated with GAMROZYNE.

CLINICAL PHARMACOLOGY

The macrolide antimicrobials as a class are weak bases and as such concentrate in some cells (such as pulmonary leukocytes). Prolonged exposure of extracellular pulmonary pathogens to macrolides appears to reflect the slow release of drug from its intracellular reservoir to the site of action, the pulmonary epithelial lining fluid (ELF). It is the ELF that is relevant to the successful treatment and control of BRD. Gamithromycin is primarily bacteriostatic at therapeutic concentrations. However, in vitro bactericidal activity has been observed at concentrations of 10 μg/mL (Mueller-Hinton broth) and after exposure to the 6-hour and 24-hour plasma samples derived from cattle dosed at 6 mg gamithromycin/kg BW.

Macrolides typically exhibit substantially higher concentrations in the alveolar macrophages and ELF as compared to concentrations observed in plasma. Gamithromycin concentrations in the ELF and ELF cells exceed the concentrations observed in the plasma. Postmortem gamithromycin concentrations in ELF exceed the MIC90 of M. haemolytica, H. somni and P. multocida through at least 72 hours after drug administration. Because M. haemolytica, P. multocida and H. somni are extracellular pathogens, drug concentrations in the ELF are considered to be clinically relevant. The postmortem area under the concentration-time curve (AUC) observed in lysed ELF cells (e. g., alveolar macrophages) are at least 300-times greater than that in the plasma. Although published studies suggest that inflammation can increase the release of drug from macrophages and neutrophils, these high concentrations in the alveolar macrophages should not be considered indicative of the magnitude or duration of response to the pathogens for which this product is indicated.

Gamithromycin administered subcutaneously in the neck of cattle at a single dosage of 6 mg/kg BW is rapidly and completely absorbed, with peak concentrations generally occurring within 1 hour after administration. Based upon plasma and lung homogenate data, the terminal half-life (T½) of gamithromycin is approximately 3 days. In vitro plasma protein binding studies show that 26% of the gamithromycin binds to plasma protein, resulting in free drug available for rapid and extensive distribution into body tissues. The free drug is rapidly cleared from the systemic circulation with a clearance rate of 712 mL/hr/kg and a volume of distribution of 25 L/kg. Dose proportionality was established based on AUC over a range of 3 mg/kg BW to 9 mg/kg BW. Biliary excretion of the unchanged drug is the major route of elimination.

MICROBIOLOGY

The minimum inhibitory concentrations (MIC's) of gamithromycin were determined for BRD isolates obtained from calves enrolled in BRD treatment field studies in the U.S. in 2004 using methods recommended by the Clinical and Laboratory Standards Institute (M31-A2). Isolates were obtained from pre-treatment nasopharyngeal swabs from each enrolled calf and from calves removed from the study due to BRD. The results are shown below in Table 1.

EFFECTIVENESS

The effectiveness of gamithromycin for the treatment of BRD associated with Mannheimia haemolytica, Pasteurella multocida and Histophilus somni was demonstrated in a field study conducted at four geographic locations in the United States. A total of 497 cattle exhibiting clinical signs of BRD were enrolled in the study. Cattle were administered gamithromycin (6 mg/kg BW) or an equivalent volume of sterile saline as a subcutaneous injection once on Day 0. Cattle were observed daily for clinical signs of BRD and were evaluated for clinical success on Day 10. The percentage of successes in cattle treated with gamithromycin (58%) was statistically significantly higher (p<0.05) than the percentage of successes in the cattle treated with saline (19%).

The effectiveness of gamithromycin for the treatment of BRD associated with M. bovis was demonstrated independently at two U.S. study sites. A total of 502 cattle exhibiting clinical signs of BRD were enrolled in the studies. Cattle were administered gamithromycin (6 mg/kg BW) or an equivalent volume of sterile saline as a subcutaneous injection once on Day 0. At each site, the percentage of successes in cattle treated with gamithromycin on Day 10 was statistically significantly higher than the percentage of successes in the cattle treated with saline (74.4% vs. 24% [p <0.001], and 67.4% vs. 46.2% [p = 0.002]). In addition, in the group of calves treated with gamithromycin that were confirmed positive for M. bovis (pre-treatment nasopharyngeal swabs), there were more calves at each site (45 of 57 calves, and 5 of 6 calves) classified as successes than as failures.

The effectiveness of gamithromycin for the control of respiratory disease in cattle at high risk of developing BRD associated with Mannheimia haemolytica and Pasteurella multocida was demonstrated in two independent studies conducted in the United States. A total of 467 crossbred beef cattle at high risk of developing BRD were enrolled in the study. Gamithromycin (6 mg/kg BW) or an equivalent volume of sterile saline was administered as a single subcutaneous injection within one day after arrival. Cattle were observed daily for clinical signs of BRD and were evaluated for clinical success on Day 10 post-treatment. In each of the two studies, the percentage of successes in the cattle treated with gamithromycin (86% and 78%) was statistically significantly higher (p = 0.0019 and p = 0.0016) than the percentage of successes in the cattle treated with saline (36% and 58%).

ANIMAL SAFETY

In a target animal safety study in healthy, six-month old beef cattle, gamithromycin was administered by subcutaneous injection at 6, 18, and 30 mg/kg bodyweight (1, 3, and 5 times the labeled dose) on Day 0, 5, and 10 (3 times the labeled administration frequency). Injection site discomfort (neck twisting, attempts to scratch or lick the injection site, and pawing at the ground) was observed in calves in the 18 mg/kg BW and 30 mg/kg BW groups at 10 minutes post-treatment following each injection. Mild to moderate injection site swelling and pathology changes consistent with inflammation were observed in the gamithromycin-treated groups. Other than injection site reactions, no clinically relevant treatment-related effects were observed.

STORAGE CONDITIONS

Store at or below 77°F (25°C) with excursions between 59-86°F (15-30°C). Use within 28 days of first puncture. If using multi-dosing equipment with a draw-off spike 4 gauge or smaller, puncture a maximum of 5 times. When using a needle larger than 16 gauge, or a draw-off spike larger than 4 gauge, discard any remaining product immediately after use.

HOW SUPPLIED

GAMROZYNE is available in three ready-to-use bottle sizes. The 100, 250 and 500 mL bottles contain sufficient solution that will treat 10, 25 and 50 head of 550 lb (250 kg) cattle respectively.

Approved by FDA under ANADA # 200-819

GAMROZYNE is a trademark of Bimeda, Inc.

Manufactured for:
Bimeda, Inc.
Le Sueur, MN 56058
Made in Canada

05/25